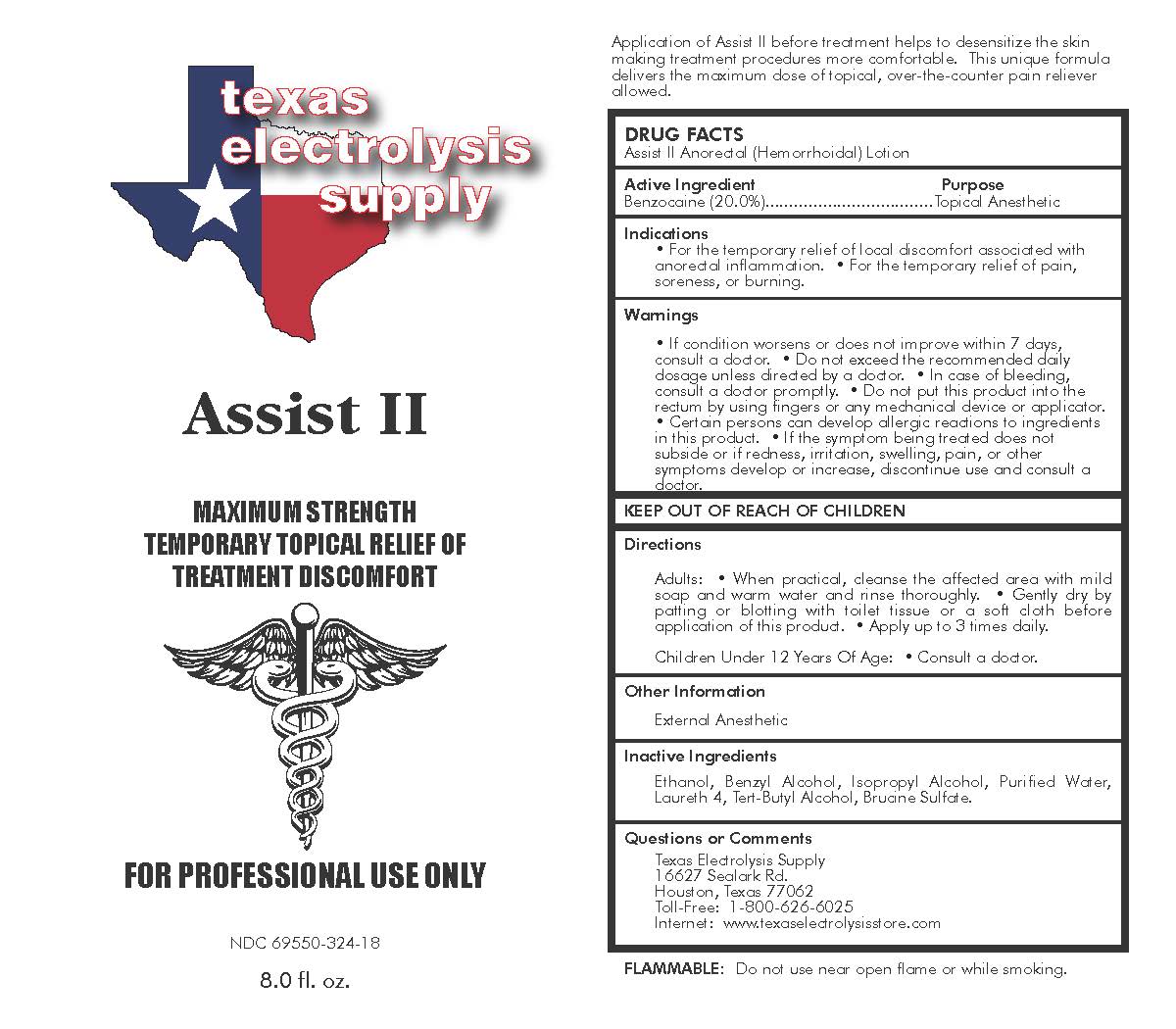 DRUG LABEL: Assist II
NDC: 69550-324 | Form: LIQUID
Manufacturer: Texas Electrolysis Supply
Category: otc | Type: HUMAN OTC DRUG LABEL
Date: 20230118

ACTIVE INGREDIENTS: BENZOCAINE 20 g/100 mL
INACTIVE INGREDIENTS: WATER; TERT-BUTYL ALCOHOL; BRUCINE SULFATE; ALCOHOL; BENZYL ALCOHOL; ISOPROPYL ALCOHOL; LAURETH-4

Drug Facts

Assist II Anorectal (Hemorrhoidal) Lotion

Active Ingredient

Benzocaine (20.0%)

Purpose

Topical Anesthetic

Indications

• For the temporary relief of local discomfort associated with anorectal inflammation. • For the temporary relief of pain, soreness, or burning.

Warnings

• If condition worsens or does not improve within 7 days, consult a doctor. • Do not exceed the recommended daily dosage unless directed by a doctor. • In case of bleeding, consult a doctor promptly. • Do not put this product into the rectum by using fingers or any mechanical device or applicator. • Certain persons can develop allergic reactions to ingredients in this product. • If the symptom, swelling, pain, or other symptoms develop or increase, discontinue use and consult a doctor.

Directions

Adults: • When practical, cleanse the affected area with mild soap and warm water and rinse thoroughly. • Gently dry by patting or blotting with toilet tissue or a soft cloth before application of this product. • Apply up to 3 times daily.

Children Under 12 Years Of Age: • Consult a doctor.

Other Information

External Anesthetic

Inactive Ingredients

Ethanol, Benzyl Alcohol, Isopropyl Alcohol, Purified Water, Laureth 4, Tert-Butyl Alcohol, Brucine Sulfate.

Questions or Comments

Texas Electrolysis Supply

16627 Sealark Rd.

Houston, Texas 77062

Toll-Free: 1-800-626-6025

Internet: www.texaselectrolysisstore.com

PACKAGE LABEL

Assist II Anorectal (Hemorrhoidal) Lotion